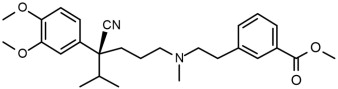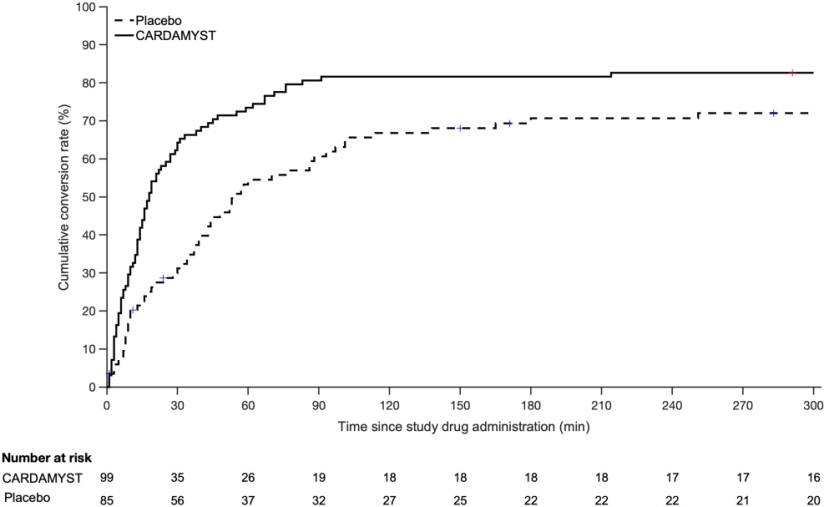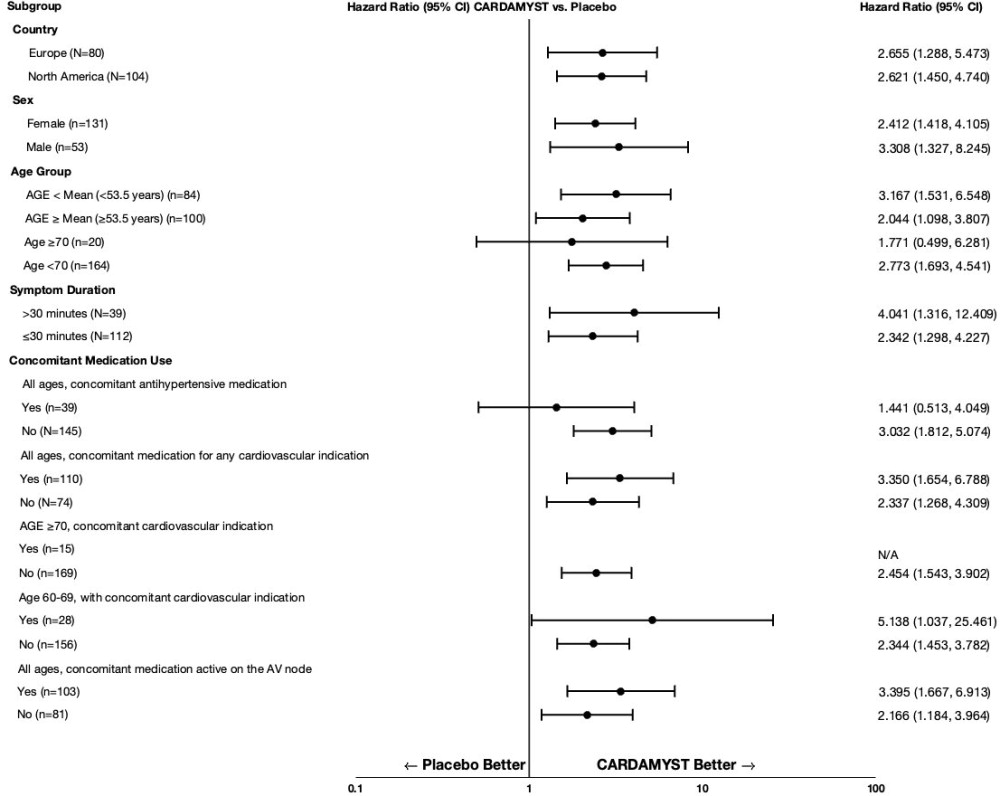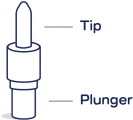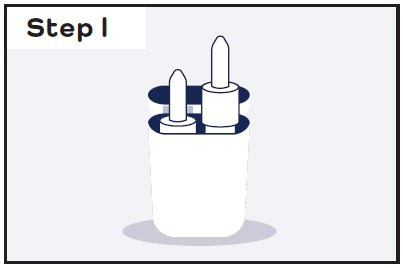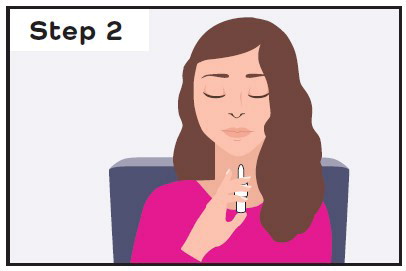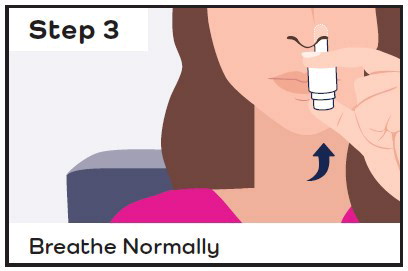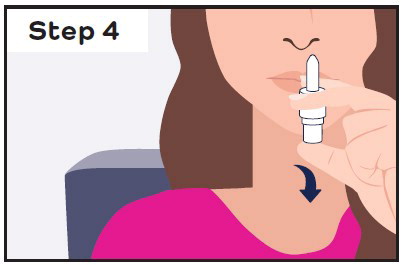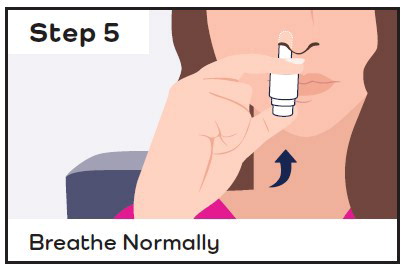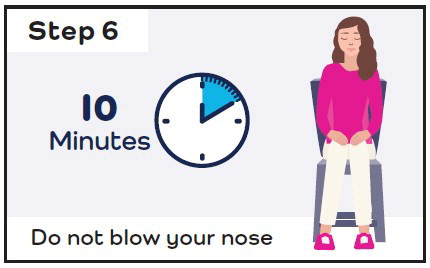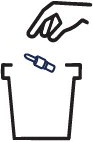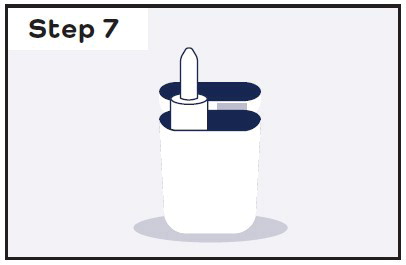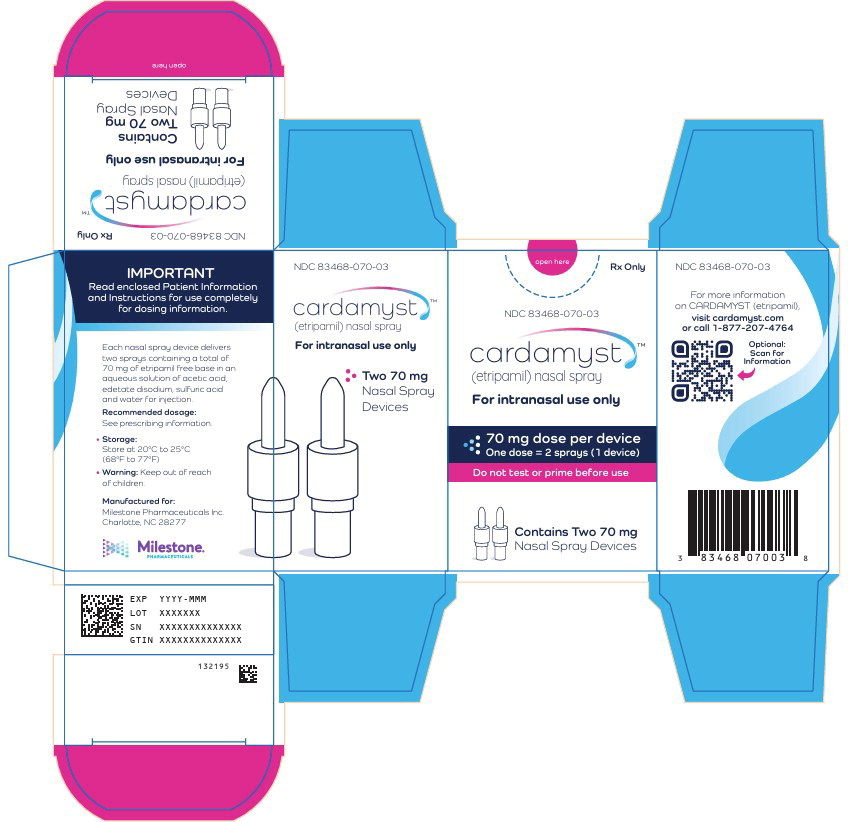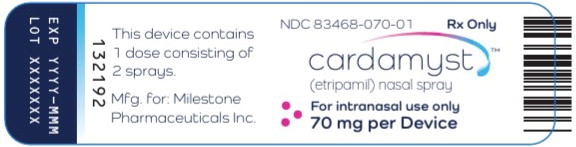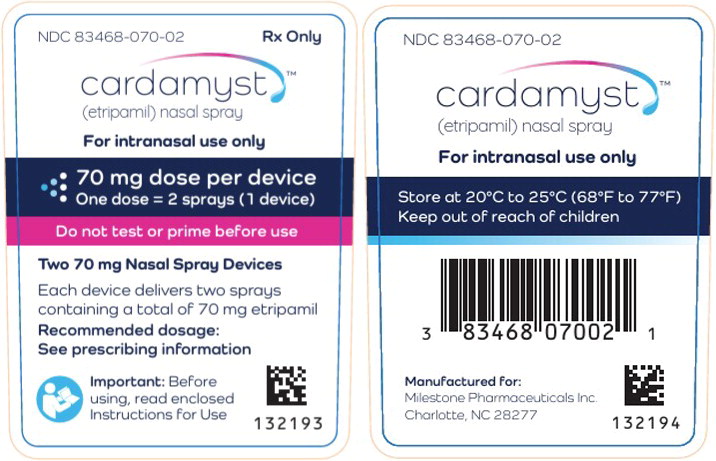 DRUG LABEL: Cardamyst
NDC: 83468-070 | Form: SPRAY
Manufacturer: Milestone Pharmaceuticals USA, Inc.
Category: prescription | Type: HUMAN PRESCRIPTION DRUG LABEL
Date: 20251208

ACTIVE INGREDIENTS: etripamil 70 mg/0.2 mL
INACTIVE INGREDIENTS: acetic acid; sulfuric acid; edetate disodium; water

HIGHLIGHTS OF PRESCRIBING INFORMATION

These highlights do not include all the information needed to use CARDAMYSTTM safely and effectively. See full prescribing information for CARDAMYSTTM.
CARDAMYSTTM (etripamil) nasal spray
Initial U.S. Approval: 2025

1 INDICATIONS AND USAGE

CARDAMYST is a calcium channel blocker indicated for the conversion of acute symptomatic episodes of paroxysmal supraventricular tachycardia (PSVT) to sinus rhythm in adults (1).

2 DOSAGE AND ADMINISTRATION

- For intranasal use only (2.1).
- Initial dosage: A dose of 70 mg is administered as two nasal sprays, one spray into each nostril. Each nasal spray device delivers two sprays. The two sprays together contain a total of 70 mg etripamil (2.1).
- Repeat dosage (if needed): Should symptoms persist for 10 minutes after administration of CARDAMYST, take a second dose of 70 mg administered as two nasal sprays, one spray into each nostril. Do not exceed 140 mg in a 24-hour period (2.1).

3 DOSAGE FORMS AND STRENGTHS

Nasal spray: 70 mg etripamil per device (3).

4 CONTRAINDICATIONS

- Hypersensitivity to CARDAMYST or any of its components (4).
- Heart failure - New York Heart Association (NYHA) Class II to IV (4).
- Wolff-Parkinson-White (WPW), Lown-Ganong-Levine (LGL) syndromes, or manifest pre-excitation (delta wave) on a 12-lead ECG (4).
- Sick sinus syndrome (except in patients with a permanent pacemaker) (4)
- Second degree atrioventricular (AV) Mobitz 2 block or higher degree of AV block (4)

5 WARNINGS AND PRECAUTIONS

- Syncope: May cause dizziness and/or syncope, especially in patients with a history of syncope. Administer in a sitting position (5.1).

6 ADVERSE REACTIONS

Most common adverse reactions (incidence > 5%) are nasal discomfort, nasal congestion, rhinorrhea, throat irritation, and epistaxis (6.1).

To report SUSPECTED ADVERSE REACTIONS, contact Milestone Pharmaceuticals USA, INC. at toll-free phone 1-877-207-4764 or FDA at 1-800-FDA-1088 or www.fda.gov/medwatch.

8 USE IN SPECIFIC POPULATIONS

- Lactation: A lactating woman should pump and discard breastmilk for 12 hours after CARDAMYST administration (8.2).

FULL PRESCRIBING INFORMATION

1 INDICATIONS AND USAGE

CARDAMYST is indicated for the conversion of acute symptomatic episodes of paroxysmal supraventricular tachycardia (PSVT) to sinus rhythm in adults.

2 DOSAGE AND ADMINISTRATION

2.1 Recommended Dosage

Administer as soon as possible after PSVT symptom onset.

Administer CARDAMYST by the nasal route only.

Each CARDAMYST device delivers two sprays for a total of 70 mg.

Recommended Dosage:

Using one nasal spray device, administer one spray into each nostril for a total initial dose of 70 mg. If symptoms persist after 10 minutes, use the second nasal spray device to administer a second dose of one spray into each nostril (70 mg total). Patients and caregivers should call their healthcare provider or seek emergency medical help if symptoms do not improve within 20 minutes after a second dose. Do not exceed 140 mg in a 24-hour period. See Instructions for Use for proper nasal spray technique.

If a full initial dose (i.e., 2 sprays, one in each nostril) is not administered due to device malfunction or misuse, the patient should wait at least 10 minutes before self-administering a second dose, if needed.

3 DOSAGE FORMS AND STRENGTHS

Nasal Spray: Clear colorless to yellow solution. 70 mg of etripamil per device.

4 CONTRAINDICATIONS

CARDAMYST is contraindicated in patients with:

- Hypersensitivity to CARDAMYST or any of its components.
- Heart failure – New York Heart Association (NYHA) Class II to IV.
- Wolff-Parkinson-White (WPW), Lown-Ganong-Levine (LGL) syndromes, or manifest pre-excitation (delta wave) on a 12-lead electrocardiogram (ECG).
- Sick sinus syndrome without a permanent pacemaker.
- Second degree atrioventricular (AV) Mobitz 2 block or higher degree of AV block.

5 WARNINGS AND PRECAUTIONS

5.1 Syncope Related to Hemodynamic Effects

Because of effects on blood pressure, heart rate, and cardiac conduction, CARDAMYST may cause dizziness and/or syncope, especially in patients with a history of syncope and high-grade AV block or sinus node dysfunction, or those with a history of syncope during an episode of PSVT. In clinical trials, a small percentage of patients (0.4%) experienced clinically significant hypotension during test dosing prior to randomization, which precluded further participation in the study. Patients with a history of hypotensive episodes or those at increased risk for hemodynamic instability should be monitored appropriately when initiating CARDAMYST.

If syncope occurs, patients should be placed in the recumbent position and treated supportively.

Patients should be cautioned about these possible adverse effects and advised to administer CARDAMYST in a sitting position, and in a location where the risk of fall is minimal.

6 ADVERSE REACTIONS

The following clinically significant adverse reactions are described elsewhere in the labeling:

- Risk of syncope [see Warnings and Precautions (5.1)]

6.1 Clinical Trials Experience

Because clinical trials are conducted under widely varying conditions, adverse reaction rates observed in the clinical trials of a drug cannot be directly compared to rates in the clinical trials of another drug and may not reflect the rates observed in practice.

The safety of CARDAMYST was evaluated using pooled data from double-blind, randomized, placebo-controlled trials including NODE-1, NODE-301 Part 1, RAPID, and RAPID Extension. A total of 321 patients were treated with CARDAMYST in randomized controlled studies.

In the RAPID and RAPID Extension studies, in which patients had the option of self-administering a second dose of CARDAMYST for a perceived episode of PSVT, the majority of patients (65%) self-administered a second dose of CARDAMYST (2x70mg).

In NODE-301 Part 1, RAPID, and RAPID Extension, to assess tolerability, a test dose(s) was given prior to randomization. A small percentage of patients failed the test dose due to hypotension (0.4%) [see Warnings and Precautions (5.1)].

The majority of treatment-related adverse reactions reported in clinical studies with CARDAMYST have been related to local reactions to, at, or near the nasal administration site, including the nose, throat, and eyes. These local reactions included nasal discomfort, nasal congestion, throat irritation, oropharyngeal pain, lacrimation, rhinorrhea, bleeding from the nose, upper-airway cough syndrome, and sneezing.

Table 1: Most frequent (≥5.0%) Adverse Reactions^1 Observed in Randomized Controlled Studies
 | Placebo N=223 % | CARDAMYST 70 mg N=235 % | CARDAMYST 2x70 mg^2 N=86 %
Nasal Discomfort | 6 | 28 | 23
Nasal Congestion | 1 | 14 | 12
Rhinorrhea | 2 | 12 | 10
Throat Irritation | 1 | 7 | 6
Epistaxis | 1 | 6 | 7
1) Adverse reactions that occurred within 24 hours of study drug administration (TEAE24h) for perceived PSVT in the double-blind, placebo-controlled studies, NODE-1, NODE-301 Part 1, RAPID and RAPID Extension that had an overall incidence of 5% or greater and where the incidence is at least 1% greater than the placebo group.
2) 2x70 mg: first administration of etripamil 70 mg followed by a second dose of etripamil 70 mg 10 minutes later if symptoms persisted.

8 USE IN SPECIFIC POPULATIONS

8.1 Pregnancy

Risk Summary

There are no available data on the use of CARDAMYST during pregnancy to inform a drug-associated risk of major birth defects, miscarriage, or other adverse maternal or fetal outcomes. Reproductive studies conducted with intravenous administration of etripamil in pregnant rats and rabbits during organogenesis did not show any evidence of fetal harm or malformations in rats at exposures up to approximately 3x the maximum concentration (Cmax) and 0.4x the AUC at the maximum recommended human dose (MRHD) and in rabbits at exposures approximately equivalent to the Cmax and 10x the AUC at the MRHD, at which maternal toxicities were observed (see Data).

The background risk of major birth defects and miscarriage for the indicated population is unknown. All pregnancies have a background risk of birth defect, loss, or other adverse outcomes. In the U.S. general population, the estimated background risk of major birth defects and miscarriage in clinically recognized pregnancies is 2%-4% and 15%-20%, respectively.

Data

Animal Data

In pregnant rats, intravenous administration of etripamil throughout the period of organogenesis did not result in any adverse effects on embryofetal development at doses up to 0.375 mg/kg/day, approximately 3x the Cmax and 0.4x the AUC at the MRHD.

In pregnant rabbits, intravenous administration of etripamil throughout the period of organogenesis did not result in embryofetal abnormalities at doses up to 0.1 mg/kg/day, approximately equivalent to the Cmax and 10x the AUC at the MRHD. Abortion in one animal was noted at the high dose of 0.1 mg/kg/day, a dose that caused maternal toxicity.

In the pre- and post-natal toxicity study in rats, intravenous administration of etripamil from gestation day 7 through the lactation period (post-partum day 20), did not show any adverse effects on pre- and postnatal development at doses up to 0.374 mg/kg/day, approximately 3x the Cmax and 0.4x the AUC at the MRHD. Post-implantation loss was noted at 0.374 mg/kg/day, a dose that also caused significant maternal toxicity, including mortality, transient adverse clinical signs, and body weight reduction.

8.2 Lactation

Risk Summary

There are no data on the presence of etripamil in human milk or animal milk. However, the structurally related compound, verapamil, is known to be present in human milk. There are no data on the effects of etripamil on the breastfed infant or on milk production. Because the presence of etripamil in breastmilk has not been characterized, and there is a potential for adverse reactions in the breastfed infant including hypotension and bradycardia, lactating women should interrupt breastfeeding and pump and discard milk for 12 hours (approximately 5 terminal half-lives) after treatment with CARDAMYST.

8.4 Pediatric Use

The safety and effectiveness of CARDAMYST have not been established in the pediatric population.

Etripamil is structurally similar to another drug in the same pharmacologic class that has been associated with a high risk of potentially non-reversible electromechanical dissociation or cardiovascular collapse in pediatric patients less than 1 year of age, including neonates.

8.5 Geriatric Use

Of the total number of patients in clinical trials of CARDAMYST, 41% (681/1662) were 60 years of age and over, and 14% (238/1662) were 70 years of age and over. No meaningful differences in safety or effectiveness were observed between these patients and younger groups.

10 OVERDOSAGE

Overdosage is expected to cause peripheral vasodilation with possible symptomatic hypotension and reflex tachycardia. AV block and /or pauses may also occur.

Treatment of overdosage should be supportive. Beta-adrenergic stimulation or parenteral administration of calcium solutions may increase calcium ion flux across the slow calcium channel. Clinically significant hypotensive reactions or high degree AV block should be treated with fluid administration or vasopressor agents, or cardiac pacing, respectively. Asystole should be handled by the usual measures including cardiopulmonary resuscitation.

It is unknown whether etripamil is dialyzable. However, the structurally related compound, verapamil cannot be removed by hemodialysis.

11 DESCRIPTION

Etripamil, the active ingredient of CARDAMYST is a calcium channel blocker.

The chemical name of etripamil is benzoic acid, 3-[2-[[(4S)-4-cyano-4-(3,4-dimethoxyphenyl)-5-methylhexyl]methylamino]ethyl]-, methyl ester.

Its molecular weight is 452.59 and its molecular formula is C27H36N2O4.

The structural formula is:

Etripamil is a colorless to slightly yellow oil. Etripamil has a pKa of 8.57 and is very soluble in methyl tert-butyl ether, freely soluble in methanol, dichloromethane and acetone, sparingly soluble in ethanol and hexane, and insoluble in water.

CARDAMYST is a spray intended for nasal administration. Each device of CARDAMYST delivers two metered sprays of etripamil with a total of 70 mg. CARDAMYST contains 350 mg/mL of etripamil and the following inactive ingredients: acetic acid, edetate disodium, sulfuric acid for pH adjustment, and water for injection.

12 CLINICAL PHARMACOLOGY

12.1 Mechanism of Action

Etripamil is an L-type calcium influx inhibitor (slow channel blocker or calcium ion antagonist). Etripamil exerts its pharmacologic effect by modulating the influx of ionic calcium across the cell membrane of the AV nodal cells as well as arterial smooth muscles and contractile myocardial cells. By interrupting reentry at the AV node, etripamil can restore sinus rhythm in patients with PSVT.

12.2 Pharmacodynamics

Cardiac Electrophysiology

Etripamil prolonged the baseline PR interval by 8% to 10% approximately 5 minutes following an intranasal dose of 70 mg. This PR interval prolongation begins to decline shortly after the etripamil maximum concentration (Cmax) and falls below the 8 to 10% threshold between 25 and 50 minutes. Etripamil mean maximum change from baseline PR interval was approximately 13% following a single 70 mg dose and 20% following two 70 mg doses in the NODE-103 trial. At a dose of 1 to 2 times the maximum recommended therapeutic dose, etripamil does not prolong the QTc interval.

Hemodynamics

In patients with induced supraventricular tachycardia in an electrophysiology laboratory, a single intranasal etripamil administration was associated with a maximal systolic blood pressure reduction of approximately 21 mm Hg with 140 mg (2 x maximum approved dose), 17 mm Hg with 105 mg (1.5 x maximum approved dose), and 3 mm Hg with 70 mg dose. No reduction in blood pressure was observed with etripamil 35 mg dose.

12.3 Pharmacokinetics

After one 70 mg dose of etripamil, mean (%CV) area under the concentration-time curve (AUC) is approximately 5461 (51.6%) ng*min/mL and the Cmax is approximately 99 (64.6%) ng/mL. After a second 70 mg dose of etripamil administered 10 minutes after the first dose, mean (%CV) AUC is approximately 7721 (50.3%) ng*min/mL and the Cmax is approximately 132 (59.1%) ng/mL.

Absorption

Etripamil median (range) time to Cmax (Tmax) is 7 minutes (3 to 20 minutes) following a single intranasal administration of 70 mg. Median Tmax is 13 minutes (3 to 35 minutes) following a second intranasal administration of 70 mg.

Distribution

Etripamil mean apparent volume of distribution ranges from approximately 2200 to 3500 L. Etripamil plasma protein binding is approximately 50%.

Elimination

Average etripamil concentration fell by approximately 60% of its peak value (Cmax) at 25 minutes and 80% of the Cmax by 60 minutes after dosing. Subsequently, concentrations decrease at a slower rate, and this decline is associated with a half-life of approximately 2.5 hours.

Metabolism: Etripamil metabolic pathways include hydrolysis, demethylation, N-dealkylation, and secondary oxidation, glucuronidation, and taurine conjugation. Etripamil is primarily metabolized by blood esterases and hepatic metabolism, primarily via CYP3A4, and CYP3A5. Etripamil contains a methyl ester which renders it metabolically sensitive to bloodborne esterases.

Excretion: After a single dose of radiolabeled intranasal etripamil 70 mg to healthy subjects, approximately 29% of the dose was recovered in urine (<0.05% unchanged), 26% was recovered in feces (<0.05% unchanged), and the remainder was recovered on nose and face tissues. Approximately 71% of the total administered dose was recovered in 7-10 days.

Specific Populations

No clinically significant differences in the pharmacokinetics of etripamil were observed based on age (19 to 56 years old), body weight (49 to 91 kg), height (157 to 194 cm), sex, or race (Caucasian, Asian, or African American). The effect of renal impairment (eGFR < 90 mL/min) or hepatic impairment (Child Pugh A, B, or C) on etripamil pharmacokinetics is unknown. It is unknown whether etripamil is dialyzable.

Drug Interaction Studies

Clinical Studies and Model-Informed Approaches

Negative chronotropic and inotropic agents: CARDAMYST was safely administered to patients taking beta blockers or calcium channel blockers. In RAPID, 107 (42%) patients were on beta blockers and 81 (32%) patients were on calcium channel blockers.

In Vitro Studies

Cytochrome P450 (CYP) Enzymes: Etripamil is a CYP3A4 and CYP3A5 substrate. Etripamil inhibits CYP2D6, CYP3A4, and CYP2C9 but does not inhibit CYP2B6 or CYP2C8. Etripamil does not induce CYP1A2, CYP2B6, or CYP3A4.

Transporter Systems: Etripamil is a substrate of P-gp and OATP1B1, but not BCRP, OATP1B3, OCT1, OCT2, OAT1, OAT3, MATE1, and MATE2-K. Etripamil inhibits P-gp and MATE1, but not BCRP, BSEP, MATE2-K, OAT1, OAT3, OATP1B1, OATP1B3, OCT1, and OCT2.

13 NONCLINICAL TOXICOLOGY

13.1 Carcinogenesis, Mutagenesis, Impairment of Fertility

Carcinogenesis

Long term carcinogenicity studies in rodents have not been conducted with etripamil.

Mutagenesis

Etripamil was not genotoxic in a bacterial reverse mutation assay, an in vitro chromosome aberration assay in human peripheral lymphocytes, and an in vivo micronucleus study in rats (IV administration).

Impairment of Fertility

In a male and female fertility study, rats were dosed once daily via intravenous administration at etripamil doses of 0.05 to 0.374 mg/kg/day. Male rats were dosed for 28 days prior to mating, and female rats were dosed for 14 days prior to mating and continuing up to day 7 of pregnancy. There was no effect on fertility of male and female rats at doses up to 0.374 mg/kg/day, approximately 3× the Cmax and 0.4× the AUC at the MRHD.

14 CLINICAL STUDIES

The RAPID study (NCT #03464019) was a randomized, double-blind, placebo-controlled, multicenter, event-driven, phase 3 study designed to evaluate the efficacy and safety of CARDAMYST in patients with a history of symptomatic PSVT. Six hundred ninety-two (692) patients were randomized 1:1 to CARDAMYST 70 mg or placebo. Patients with an episode of perceived PSVT were to self-administer the study drug intranasally in a medically unsupervised setting and self-administer a second dose of the study drug if symptoms persisted at 10 minutes after the first dose. Continuously obtained electrocardiographic data during the episode of PSVT were blindly adjudicated. The primary endpoint was time-to-conversion of confirmed PSVT to sinus rhythm for at least 30 seconds within 30 minutes of the first dose.

Of the 692 randomized patients, 255 patients perceived an episode of PSVT and self-administered the study drug; 184 (72%) episodes were confirmed by blinded adjudication to be PSVT. Patients had a median age of 54 years (range 19 to 78 years) and were 71% female, 93% Caucasian, 3% Black and 4% other. Sixty-three percent (63%) of patients with confirmed PSVT episode were taking concomitant beta blocker or calcium channel blocker.

In the study's primary analysis, patients with confirmed episodes of PSVT, Kaplan-Meier Estimates of those who converted to sinus rhythm within 30 minutes were 64% and 31% for CARDAMYST and placebo, respectively, with a hazard ratio of 2.6 [95% CI: (1.7, 4.2)], p-value <0.001. Median time-to-conversion was 17.2 minutes (95% CI: 13.4, 26.5) with CARDAMYST versus 53.5 minutes (95% CI: 38.7, 87.3) with placebo. Kaplan-Meier estimates of conversion remained in favor of CARDAMYST at 300 minutes; hazard ratio 1.7 [95% CI: (1.2, 2.4)].

Kaplan-Meier plot of estimated probabilities of achieving sinus rhythm following treatment with CARDAMYST are shown in Figure 1.

Figure 1: RAPID Primary Efficacy Outcome Kaplan Meier Curve: Conversion to Sinus Rhythm in the Patient Population with Confirmed PSVT^1

1) 71/255 (28%) patients who self-administered CARDAMYST for a perceived episode of PSVT did not have confirmed PSVT and are excluded.

Seventy-one (71) of 255 (28%) patients who self-administered CARDAMYST for a perceived episode of PSVT did not have PSVT confirmed due to missing ECG data (4%), resolution of PSVT prior to dosing (5%), or other rhythm diagnoses (19%). In an analysis assuming all 71 of these patients did not convert, the Kaplan-Meier estimates for conversion to sinus rhythm within 30 minutes were 50% and 23% for the CARDAMYST and placebo groups, respectively, with a hazard ratio of 2.6 [95% CI: (1.6, 4.1)].

In RAPID, the results for the primary efficacy endpoint were generally consistent across major subgroups including geographic region, sex, age group, concomitant medications, and duration from onset of symptoms to first dose (Figure 2).

Figure 2: Conversion to Sinus Rhythm at 30 Minutes Hazard Ratios by Baseline Characteristics - RAPID Study

16 HOW SUPPLIED/STORAGE AND HANDLING

16.1 How Supplied

CARDAMYST is supplied in cartons (NDC 83468-070-03) of 2 disposable nasal spray devices contained in a plastic carrying case.

Each nasal spray device delivers two sprays containing a total of 70 mg etripamil.

16.2 Storage and Handling

Store at 20°C to 25°C (68°F to 77°F), with excursions permitted from 15°C to 30°C (59°F to 86°F) (see USP Controlled Room Temperature).

Do not test spray, prime or press the plunger before use. Discard the CARDAMYST device after use.

17 PATIENT COUNSELING INFORMATION

Advise the patient to read the FDA-approved patient labeling (Patient Information and Instructions for Use).

Important Treatment Instructions

Instruct patients and caregivers on PSVT symptoms and the timing of administration in relation to the onset of the episode of PSVT. Instruct patients and caregivers on what to observe following administration, and what would constitute an outcome requiring medical attention. Instruct patients and caregivers to call their healthcare provider or seek emergency medical help if symptoms do not improve within 20 minutes after a second dose.

Administration Information

Instruct patients and caregivers not to test or prime before use. Instruct patients and caregivers to discard the CARDAMYST device after use.

Lactation

Advise lactating women to pump and discard breastmilk for 12 hours after CARDAMYST administration in order to minimize exposure to a breastfed infant [see Use in Specific Populations (8.2)].

Manufactured for: Milestone Pharmaceuticals USA, Inc. 6210 Ardrey Kell Road, Suite 650, Charlotte, NC, 28277

PATIENT INFORMATION
CARDAMYST™ (kar da mist)
(etripamil)
nasal spray

What is CARDAMYST?
CARDAMYST is a prescription medicine used to help restore normal heart rhythm in adults who have symptoms of sudden episodes of fast heartbeat called paroxysmal supraventricular tachycardia (PSVT).
It is not known if CARDAMYST is safe and effective in children.

Do not use CARDAMYST if you:

- are allergic to CARDAMYST or to any of its ingredients. See the end of this leaflet for a complete list of ingredients in CARDAMYST.
- have limitations in activities due to heart failure (moderate to severe heart failure).
- have Wolff-Parkinson-White (WPW) syndrome, Lown-Ganong-Levine (LGL) syndrome, or an abnormal heart rhythm pattern called pre-excitation (delta wave) on an electrocardiogram (ECG).
- have sick sinus syndrome without a permanent pacemaker.
- have second degree or higher atrioventricular (AV) block.

Before using CARDAMYST, tell your healthcare provider about all of your medical conditions, including if you:

- have a history of fainting.
- have low blood pressure.
- are pregnant or plan to become pregnant. It is not known if CARDAMYST will harm your unborn baby.
- are breastfeeding or plan to breastfeed. It is not known if CARDAMYST passes into your breast milk. You should stop breastfeeding for 12 hours after treatment with CARDAMYST. During this time, pump and throw away your breast milk. Talk to your healthcare provider about the best way to feed your baby after using CARDAMYST.

Tell your healthcare provider about all the medicines you take, including prescription and over-the-counter medicines, vitamins, and herbal supplements.

How should I use CARDAMYST?

- Read the Instructions for Use that comes with CARDAMYST for information about the right way to use CARDAMYST.
- Use CARDAMYST exactly as prescribed by your healthcare provider.
- CARDAMYST is for use in the nose only.
- Each CARDAMYST device contains 1 dose consisting of 2 sprays (1 spray in each nostril).
- Do not test, prime, or press the plunger before use. The nasal spray device is ready for use.
- Use CARDAMYST as soon as possible after your PSVT symptoms begin.
- While sitting, insert the CARDAMYST device into the nostril and spray one spray in each nostril by pressing the plunger firmly and quickly all the way up and releasing it between each spray.
- Stay seated and keep your head straight for 10 minutes.
- If you still have symptoms after 10 minutes, give a second dose (1 spray in each nostril) with a new CARDAMYST device.
- If your symptoms do not improve within 20 minutes after your second dose, call your healthcare provider or get emergency medical help right away.
- If you do not receive the full first dose (1 spray in each nostril) because the device did not work or was used incorrectly, wait at least 10 minutes before giving a second dose, if needed.
- Do not use more than 2 CARDAMYST devices (140 mg) within a 24-hour period.
- Do not re-use the CARDAMYST device. Throw away (discard) the CARDAMYST device after use.
- If you use too much CARDAMYST, call your healthcare provider or go to the nearest hospital emergency room right away.

What are the possible side effects of CARDAMYST?
CARDAMYST may cause serious side effects, including:

- Fainting due to CARDAMYST effects on blood pressure, heart rate, and electrical activity of the heart. CARDAMYST may cause dizziness and fainting, especially in people with a history of fainting and certain heart problems, or people with a history of fainting during an episode of PVST. Use CARDAMYST while sitting in a safe area where you will not fall if you become dizzy or lightheaded. Lie down if you feel dizzy or lightheaded after using CARDAMYST. If fainting occurs after using CARDAMYST, caregivers should place you on your back and seek medical help.

The most common side effects of CARDAMYST include:

- nasal discomfort
- nasal congestion
- runny nose

- throat irritation
- nosebleed

These are not all of the possible side effects of CARDAMYST.
Call your doctor for medical advice about side effects. You may report side effects to FDA at 1-800-FDA-1088.

How should I store CARDAMYST?

- Store CARDAMYST at room temperature between 68°F to 77°F (20°C to 25°C).

Keep CARDAMYST and all medicines out of the reach of children.

General information about the safe and effective use of CARDAMYST.
Medicines are sometimes prescribed for purposes other than those listed in a Patient Information leaflet. Do not use CARDAMYST for a condition for which it was not prescribed. Do not give CARDAMYST to other people, even if they have the same symptoms that you have. It may harm them. You can ask your pharmacist or healthcare provider for information about CARDAMYST that is written for health professionals.

What are the ingredients in CARDAMYST?
Active ingredient: etripamil
Inactive ingredients: acetic acid, edetate disodium, sulfuric acid and water for injection.
Manufactured for: Milestone Pharmaceuticals USA, Inc., 6210 Ardrey Kell Road, Suite 650, Charlotte, NC, 28277
For more information about CARDAMYST, visit cardamyst.com or call 1-844-805-5810.

This Patient Information has been approved by the U.S. Food and Drug Administration.

Issued: December 2025

INSTRUCTIONS FOR USE

Cardamyst™ [kar da mist]

(etripamil) nasal spray

This Instructions for Use contains information on how to use CARDAMYST nasal spray.

Important Information You Need to Know Before Using CARDAMYST

- For use in the nose only.
- Each CARDAMYST device contains 1 dose consisting of 2 sprays (1 spray in each nostril). Do not press the CARDAMYST device plunger until you are ready to deliver a dose.
- Check the expiration date (‘EXP’) before using.
- Do not test or prime before use. The nasal spray device is ready for use.
- CARDAMYST may cause dizziness. Use CARDAMYST while sitting in a safe area where you will not fall if you become dizzy or lightheaded.
- If you do not get the full first dose, wait 10 minutes before using another device.
- Do not re-use the CARDAMYST device. Throw away (discard) the CARDAMYST device after use.

CARDAMYST Device

Preparing the Dose | Using CARDAMYST Nasal Spray
Remove the CARDAMYST device from the carrying case:; - Each carrying case contains 2 CARDAMYST devices. Each CARDAMYST device contains 1 dose consisting of 2 sprays (1 spray for each nostril). - Open the lid and carefully remove 1 nasal spray device from the carrying case. | Sit down and hold the nasal spray device in your hand:; - Hold the CARDAMYST device in an upright position as shown with your thumb on the bottom of the plunger and the tip between your index and middle fingers. - Do not press the plunger yet. | Insert the nasal spray device into the first nostril and spray:; - Keep your head straight. - Insert the tip of the nasal spray device into 1 nostril until your index and middle finger are touching the bottom of your nose. - Using your thumb, press the plunger firmly and quickly all the way up. - Breathe normally. Avoid inhaling deeply.
Using CARDAMYST Nasal Spray (continued)
Release the plunger:; - Completely release the plunger. - Remove the nasal spray device from the first nostril. | Insert the same nasal spray device into the second nostril and spray right away:; - With the same nasal spray device, repeat Steps 3 and 4 in the second nostril right away. - Breathe normally. Avoid inhaling deeply. | Stay seated and keep your head straight for 10 minutes:; - For CARDAMYST to work right away, keep your head straight for 10 minutes, as shown. - When medicine drips out, wipe your nose. - Do not blow your nose for 10 minutes. - Throw away (discard) the CARDAMYST device after use.
 | If you continue to have symptoms after 10 minutes:; - Repeat Steps 1 to 6 with a new CARDAMYST device. - If your symptoms have not improved within 20 minutes after your second dose, call your healthcare provider or get emergency medical help right away. - Do not use more than 2 CARDAMYST devices (140 mg) within a 24 hour period. - Replace the used CARDAMYST device with a new one right after use, so you will have a new nasal spray device in case you need it.

Storing CARDAMYST

Store CARDAMYST at room temperature between 20°C to 25°C (68°F to 77°F). |  | Keep CARDAMYST and all medicines out of the reach of children.

For more information about CARDAMYST, visit cardamyst.com or call 1-844-805-5810.

Manufactured for: Milestone Pharmaceuticals USA, Inc., 6210 Ardrey Kell Road, Suite 650, Charlotte, NC 28277

This Instructions for Use has been approved by the U.S. Food and Drug Administration. Issued: December 2025

Principal Display Panel – 70 mg Carton Label

open here

Rx Only

NDC 83468-070-03

cardamyst™
(etripamil) nasal spray

For intranasal use only

70 mg dose per device
One dose = 2 sprays (1 device)

Do not test or prime before use

Contains Two 70 mg
Nasal Spray Devices

Principal Display Panel – 70 mg Device Label

NDC 83468-070-01 Rx Only

cardamyst™
(etripamil) nasal spray

For intranasal use only

70 mg per Device

Principal Display Panel – 70 mg Container Label

NDC 83468-070-02 Rx Only

cardamyst™
(etripamil) nasal spray

For intranasal use only

70 mg dose per device
One dose = 2 sprays (1 device)

Do not test or prime before use

Two 70 mg Nasal Spray Devices

Each device delivers two sprays
containing a total of 70 mg etripamil
Recommended dosage:
See prescribing information

Important: Before
using, read enclosed
Instructions For Use